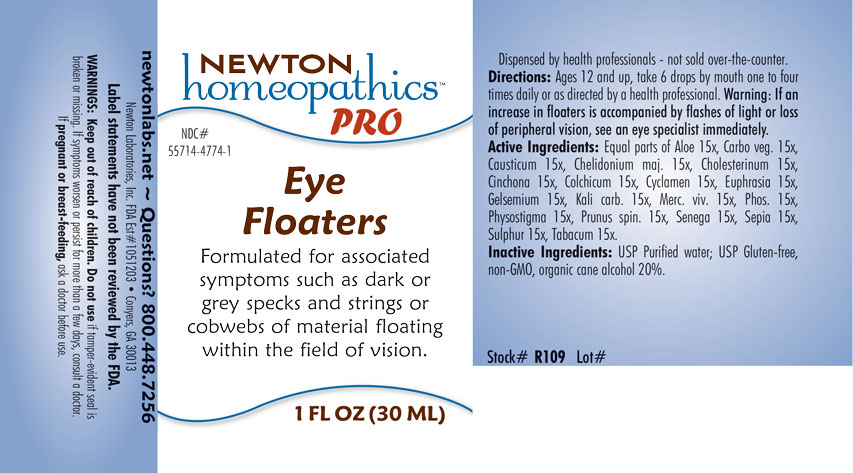 DRUG LABEL: Eye Floaters
NDC: 55714-4774 | Form: LIQUID
Manufacturer: Newton Laboratories, Inc.
Category: homeopathic | Type: HUMAN OTC DRUG LABEL
Date: 20201203

ACTIVE INGREDIENTS: ALOE 15 [hp_X]/1 mL; CAUSTICUM 15 [hp_X]/1 mL; CHELIDONIUM MAJUS 15 [hp_X]/1 mL; CHOLESTEROL 15 [hp_X]/1 mL; CINCHONA OFFICINALIS BARK 15 [hp_X]/1 mL; COLCHICUM AUTUMNALE BULB 15 [hp_X]/1 mL; CYCLAMEN PURPURASCENS TUBER 15 [hp_X]/1 mL; EUPHRASIA STRICTA 15 [hp_X]/1 mL; GELSEMIUM SEMPERVIRENS ROOT 15 [hp_X]/1 mL; POTASSIUM CARBONATE 15 [hp_X]/1 mL; MERCURY 15 [hp_X]/1 mL; PHOSPHORUS 15 [hp_X]/1 mL; PHYSOSTIGMA VENENOSUM SEED 15 [hp_X]/1 mL; PRUNUS SPINOSA FLOWER BUD 15 [hp_X]/1 mL; POLYGALA SENEGA ROOT 15 [hp_X]/1 mL; SEPIA OFFICINALIS JUICE 15 [hp_X]/1 mL; SULFUR 15 [hp_X]/1 mL; TOBACCO LEAF 15 [hp_X]/1 mL; ACTIVATED CHARCOAL 15 [hp_X]/1 mL
INACTIVE INGREDIENTS: WATER; ALCOHOL

EyeFl 4774L

INDICATIONS & USAGE SECTION

Formulated for associated symptoms such as dark or grey specks and strings or cobwebs of material floating within the field of vision.

DOSAGE & ADMINISTRATION SECTION

Directions: Ages 12 and up, take 6 drops by mouth one to four times daily or as directed by a health professional. Warning: If an increase in floaters is accompanied by flashes of light or loss of peripheral vision, see and eye specialist immediately.

OTC - ACTIVE INGREDIENT SECTION

Equal parts of Aloe 15x, Carbo vegetabilis 15x, Causticum 15x, Chelidonium majus 15x, Cholesterinum 15x, Cinchona officinalis 15x, Colchicum autumnale 15x, Cyclamen europaeum 15x, Euphrasia, Gelsemium sempervirens 15x, Kali carbonicum 15x, Mercurius vivus 15x, Phosphorus 15x, Physostigma venenosum 15x, Prunus spinosa 15x, Senega officinalis 15x, Sepia 15x, Sulphur 15x, Tabacum 15x.

OTC - PURPOSE SECTION

Formulated for associated symptoms such as dark or grey specks and strings or cobwebs of material floating within the field of vision.

INACTIVE INGREDIENT SECTION

Inactive Ingredients: USP Purified Water; USP Gluten-free, non-GMO, organic cane alcohol 20%.

QUESTIONS SECTION

newtonlabs.net - Questions? 800.448.7256

Newton Laboratories, Inc. FDA Est # 1051203 Conyers, GA 30013

WARNINGS SECTION

WARNINGS: Keep out of reach of children. Do not use if tamper-evident seal is broken or missing. If symptoms worsen or persist for more than a few days, consult a doctor. If pregnant or breast-feeding, ask a doctor before use.

OTC - PREGNANCY OR BREAST FEEDING SECTION

If pregnant or breast-feeding, ask a doctor before use.

OTC - KEEP OUT OF REACH OF CHILDREN SECTION

Keep out of reach of children.